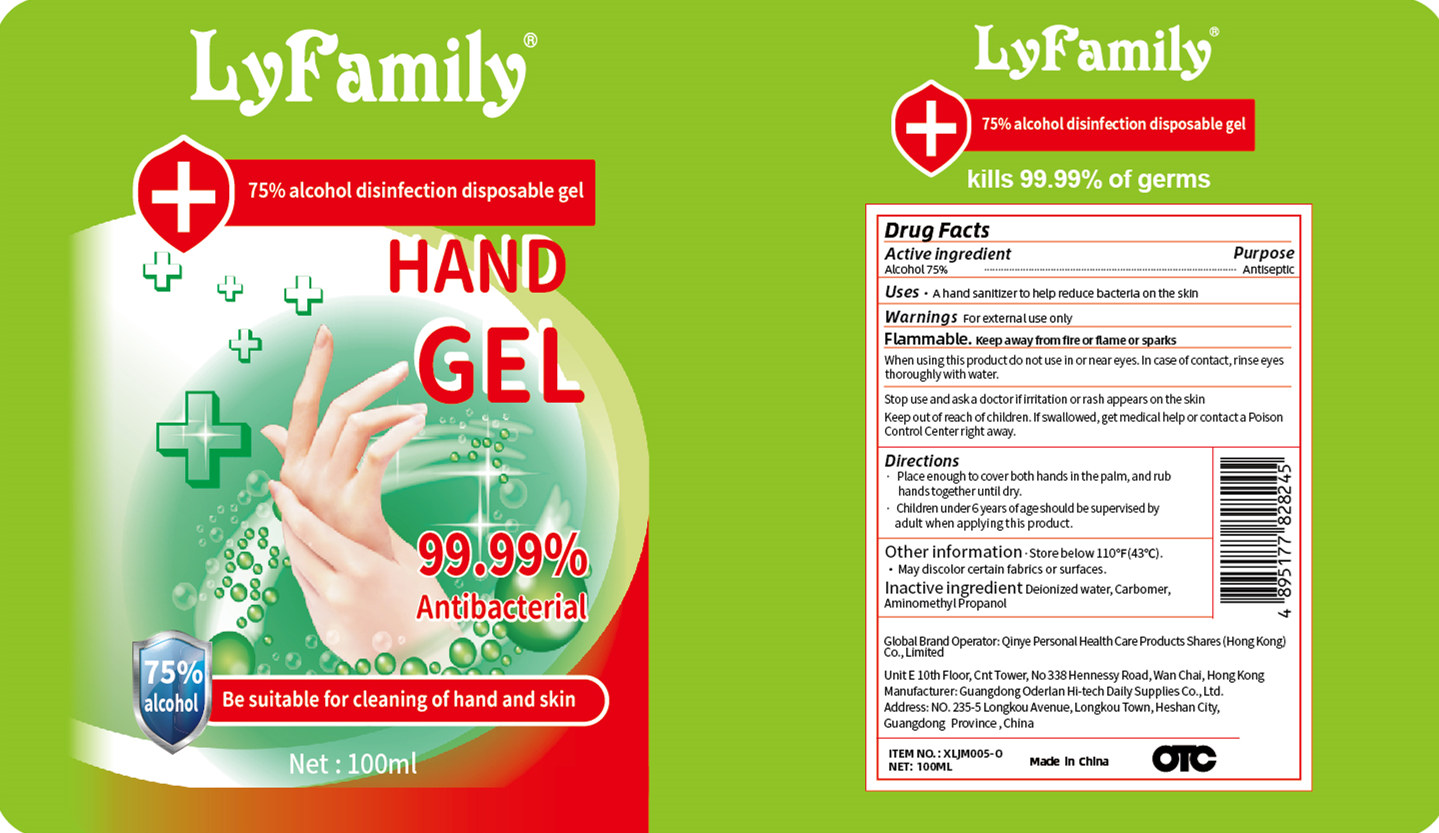 DRUG LABEL: LyFamily 75% alcohol disinfection disposable gel
NDC: 40397-002 | Form: GEL
Manufacturer: Guangdong Oderlan Hi-Tech Daily Supplies Co., Ltd.
Category: otc | Type: HUMAN OTC DRUG LABEL
Date: 20200430

ACTIVE INGREDIENTS: ALCOHOL 75 mL/100 mL
INACTIVE INGREDIENTS: AMINOMETHYLPROPANOL; WATER; CARBOMER COPOLYMER TYPE A (ALLYL PENTAERYTHRITOL CROSSLINKED)

DOSAGE AND ADMINISTRATION

Keep away from fire or flame.Store below 110*F(43*C).

INACTIVE INGREDIENT

Carbomer

Aminomethyl Propanol

Deionized Water

INDICATIONS AND USAGE

Place enough to cover both hands in the palm, and rub hands togetheruntil dry.
Children under6years ofageshould be supervised by adult when applyingthis product.

ACTIVE INGREDIENT

Alcohol

keep out of children

PURPOSE

Disinfection
Sterilization
No Rinseing

Stop use and aska doctor if iritation or rash appears on the skin Keep outof reach of children. If swallowed, get medical help or contacta Poison Control Center right away.